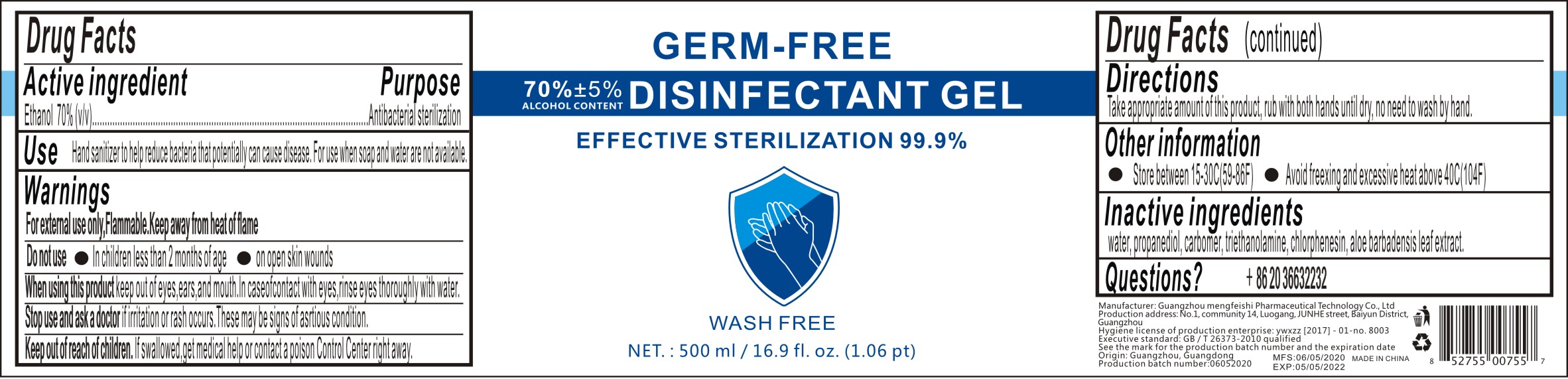 DRUG LABEL: Germ Free Disinfectant Gel
NDC: 77311-016 | Form: GEL
Manufacturer: Guangzhou Mengfeishi Pharmaceutical Technology Co., Ltd.
Category: otc | Type: HUMAN OTC DRUG LABEL
Date: 20200521

ACTIVE INGREDIENTS: ALCOHOL 70 mL/100 mL
INACTIVE INGREDIENTS: WATER; PROPANEDIOL; CARBOMER HOMOPOLYMER, UNSPECIFIED TYPE; TROLAMINE; CHLORPHENESIN; ALOE VERA LEAF

Active Ingredient

Ethanol 70% (v/v)

Purpose

Antibacterial sterilization

Use

Hand sanitizer to help reduce bacteria that potentially can cause disease. For use when soap and water are not available.

Warnings

For external use only, Flammable. Keep away from heat of flame

Do not use

In children less than 2 months of age

On open skin wounds

When using this product

Keep out of eyes, ears, and mouth. In case of contact with eyes, rinse eyes thoroughly with water.

Stop use and ask a doctor

If irritation or rash occurs. These may be signs of asrtious condition.

Keep out of reach of children.

If swallowed, get medical help or contact a poison Control Center right away.

Directions

Take appropriate amount of this product, rub with both hands until dry, no need to wash by hand.

Other information

Store between 15-30C (59-86F)

Avoid freexing and excessive heat above 40C(104F)

Inactive ingredients

water, propanediol, carbomer, triethanolamine, chlorphenesin, aloe barbadensis leaf extract.

Questions?

+83 20 36632232